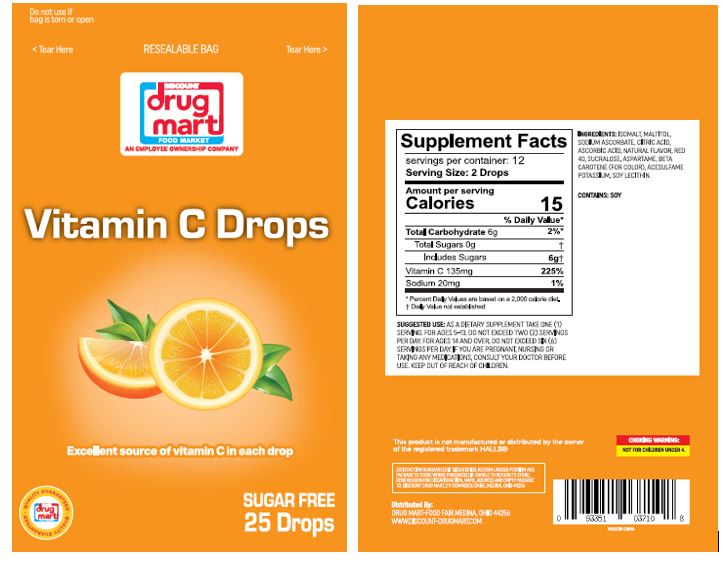 DRUG LABEL: DISCOUNT DRUG MART
NDC: 53943-509 | Form: LOZENGE
Manufacturer: DISCOUNT DRUG MART
Category: otc | Type: HUMAN OTC DRUG LABEL
Date: 20250903

ACTIVE INGREDIENTS: MENTHOL 2.7 mg/1 1
INACTIVE INGREDIENTS: ISOMALT; MALTITOL; LECITHIN, SOYBEAN; WATER; FD&C RED NO. 40; ACESULFAME POTASSIUM; ASPARTAME; SODIUM ASCORBATE; CITRIC ACID MONOHYDRATE; BETA CAROTENE; ASCORBIC ACID

DDM-MGC-YNBY Vita-C Drops 30

Active Ingredient(s)

Menthol 2.7

Purpose

Purposes cough suppressant, oral anesthetic

Use

temporary relieves: ■ cough due to cold ■ occasional minor irritation or sore throat

Warnings

Sore throat warning: If sore throat is severe, persists for more than 2 days, is accompanied or follow headache, rash, swelling, nausea, or vomiting, consult a doctor promptly. These may be serious.

Ask a doctor before use if you have: ■ persistent or chronic cough such as occurs with smoking, asthma, or emphysema ■ cough accompanied by excessive phlegm (mucus).

Stop use and ask a doctor if ■ cough persists for more than 1 week, tends to recur, or is accompained by fever, rash, or persistent headache. These could be signs of a serius condition. ■ sore mouth does not improve in 7 days ■ irritation, pain, or redness persists or worsens.

Keep out of reach of children.

Directions

■ adults and children 5 years and over: dissolve 1 drop slowly in the mouth. Repeat every 2 hours as needed.

■ children under 5 years: ask a doctor.

Other information

■ 10 calories per drop ■ contains: SOY.

Inactive ingredients

Isomalt, sodium ascorbate, citric acid, ascorbic acid, natural flavor, FD&C red 40, apartame, beta carotene, acesulfame potassium, maltitol, soy lecithin

QUESTIONS

www.discount-drugmart.com

Package Label - Principal Display Panel

25 Drops NDC: 53943-509-25